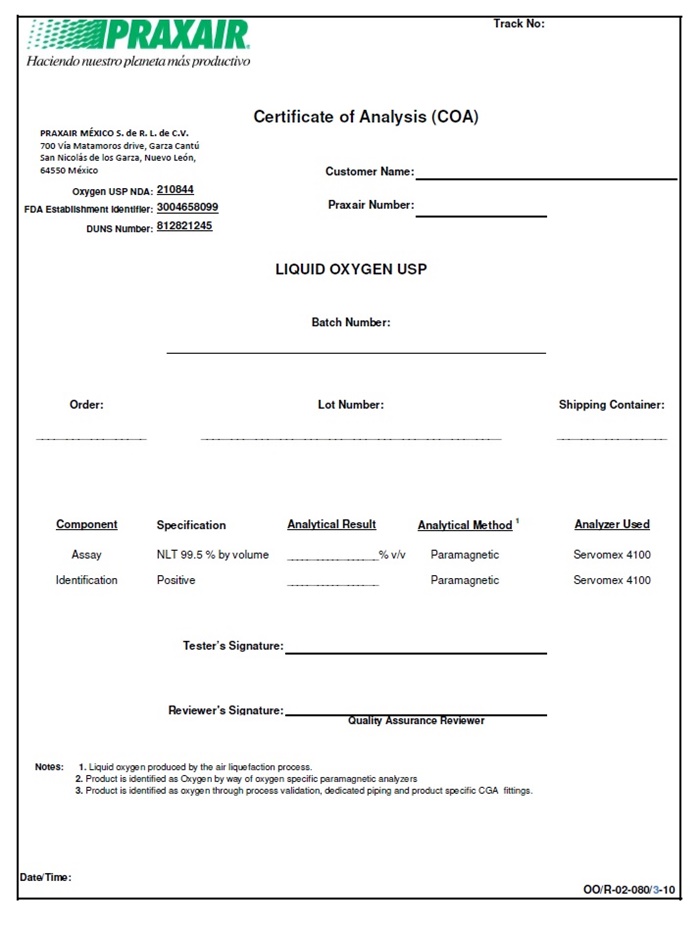 DRUG LABEL: Oxygen
NDC: 80268-001 | Form: GAS
Manufacturer: Praxair Mexico, S. de R.L. de C.V
Category: prescription | Type: HUMAN PRESCRIPTION DRUG LABEL
Date: 20211109

ACTIVE INGREDIENTS: OXYGEN 990 mL/1 L

Santa Maria Oxygen

Oxygen

PRAXAIR Track No:

Haciendo nuestro planeta mds productive

Certificate of Analysis (COA)

PRAXAIR MEXICO S. de R.L. de C.V.

700 Via Matamoros drive, Garza Cantu

San Nicolas de los Garza, Nuevo Leon,

64550 Mexico

Oxygen USP NDA: 210844 Customer Name:

FDA Establishment Identifier: 3004658099 Praxair Number:

DUNS Number: 812821245

LIQUID OXYGEN USP

Batch Number:

Order: Lot Number: Shipping Container:

Component Specification Analytical Result Analytical Method^1 Analyzer Used

Assay NLT 99.5% by volume ________%v/v Paramagnetic Servomex 4100

Identification Positive _________ Paramagnetic Servomex 4100

Tester’s Signature: __________________________

Reviewer’s Signature: _________________________

Quality Assurance Reviewer

Notes:1. Liquid oxygen produced by the air liquefaction process.

2. Product is identified as Oxygen by way of oxygen specific paramagnetic analyzers

3. Product is identified as oxygen through process validation, dedicated piping and product specific CGA fittings.

Date/Time: _______________________ OO/R-02-080/3-10